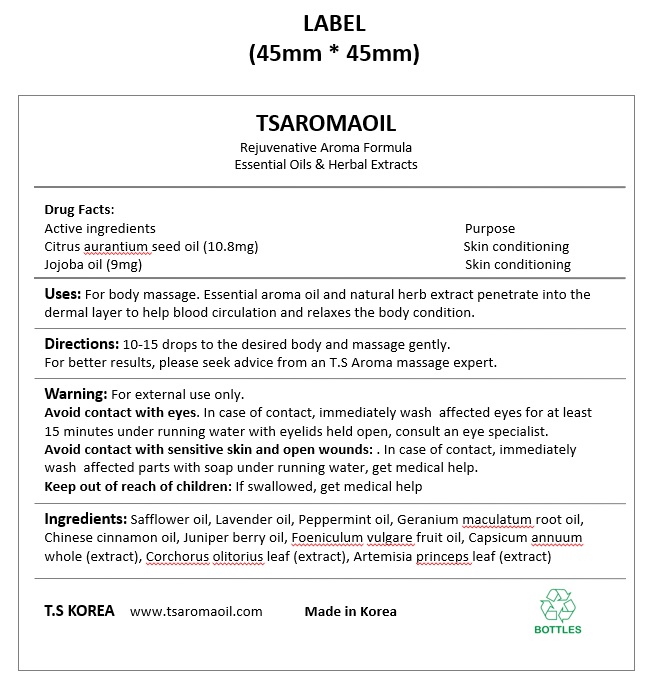 DRUG LABEL: TSAROMAOIL
NDC: 83911-201 | Form: OIL
Manufacturer: TS KOREA
Category: otc | Type: HUMAN OTC DRUG LABEL
Date: 20241231

ACTIVE INGREDIENTS: JOJOBA OIL 9 mg/100 mL; CITRUS AURANTIFOLIA SEED OIL 10.8 mg/100 mL
INACTIVE INGREDIENTS: GERANIUM MACULATUM ROOT OIL; FOENICULUM VULGARE FRUIT OIL; CORCHORUS OLITORIUS LEAF; CHINESE CINNAMON OIL; SAFFLOWER OIL; LAVENDER OIL; JUNIPER BERRY OIL; ARTEMISIA PRINCEPS LEAF; CAPSICUM ANNUUM WHOLE; PEPPERMINT OIL

ACTIVE INGREDIENT

Citrus aurantium seed oil (10.8mg) - skin conditioning

Jojoba oil (9mg) - skin cinditioning

INACTIVE INGREDIENT

Safflower oil, Lavender oil, Peppermint oil, Geranium maculatum root oil, Chinese cinnamon oil, Juniper berry oil, Foeniculum vulgare fruit oil, Capsicum annuum whole (extract), Corchorus olitorius leaf (extract), Artemisia princeps leaf (extract)

DOSAGE AND ADMINISTRATION

10-15 drops to the desired body and massage gently.

INDICATIONS AND USAGE

10-15 drops to the desired body and massage gently.

For better results, please seek advice from an T.S Aroma massage expert.

PURPOSE

For body massage

Keep out of reach of children: If swallowed, get medical help

WARNINGS

Warning: For external use only.

Avoid contact with eyes. In case of contact, immediately wash affected eyes for at least 15 minutes under running water with eyelids held open, consult an eye specialist.

Avoid contact with sensitive skin and open wounds: . In case of contact, immediately wash affected parts with soap under running water, get medical help.

Keep out of reach of children: If swallowed, get medical help